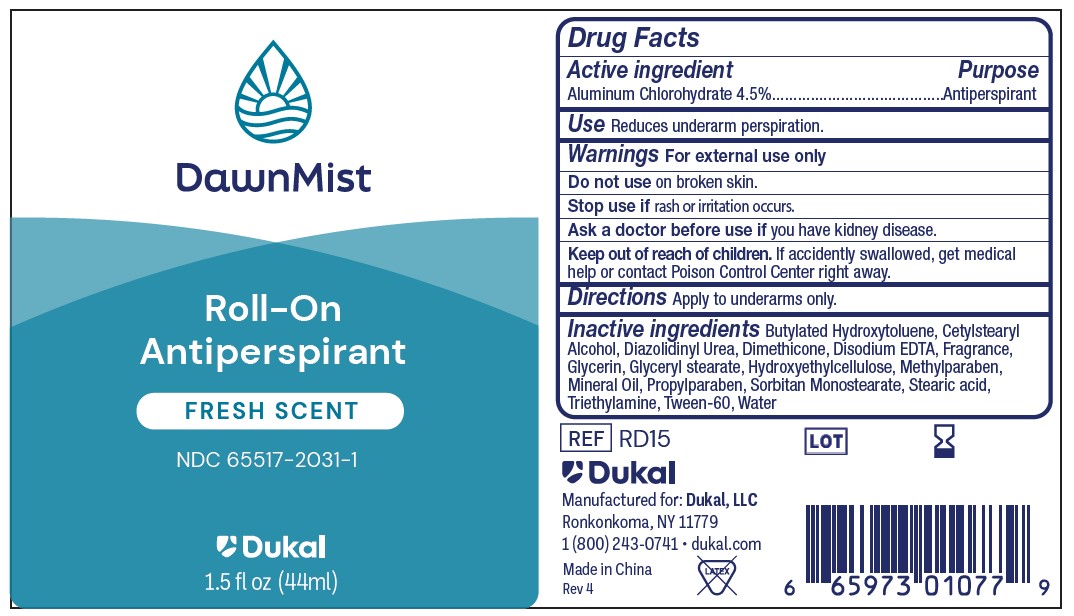 DRUG LABEL: DawnMist Antiperspirant
NDC: 65517-2031 | Form: LOTION
Manufacturer: Dukal LLC
Category: otc | Type: HUMAN OTC DRUG LABEL
Date: 20241219

ACTIVE INGREDIENTS: ALUMINUM CHLOROHYDRATE 45 mg/1 mL
INACTIVE INGREDIENTS: DIMETHICONE; CETOSTEARYL ALCOHOL; POLYSORBATE 60; TRIETHYLAMINE; PROPYLPARABEN; GLYCERYL MONOSTEARATE; BUTYLATED HYDROXYTOLUENE; MINERAL OIL; SORBITAN MONOSTEARATE; DIAZOLIDINYL UREA; EDETATE DISODIUM; METHYLPARABEN; STEARIC ACID; WATER; GLYCERIN; HYDROXYETHYL CELLULOSE, UNSPECIFIED

DawnMist Roll-On Antiperspirant 4.5% - Fresh Scent

Active Ingredient

Aluminum Chlorohydrate 4.5%

Purpose

Antiperspirant

Use

Reduces underarm perspiration

Warnings

For external use only.

Do not use on broken skin

Ask a doctor before use if you have kidney disease.

Keep out of reach of children. If accidently swallowed, get medical help or contact Poison Control Center right away.

Directions

Apply to underarms only.

Inactive ingredients

Butylated Hydroxytoluene, Cetylstearyl Alcohol, Diazolidinyl Urea, Dimethicone, Disodium EDTA, Fragrance, Glycerin, Glyceryl stearate, Hydroxyethylcellulose, Methylparaben, Mineral Oil, Propylparaben, Sorbitan Monostearate, Stearic acid, Triethylamine, Tween-60, Water

PACKAGE LABEL

DawnMist

Roll-On

Antiperspirant

Fresh Scent

NDC 65517-2031-1

Dukal

1.5FL.OZ. (44ml)